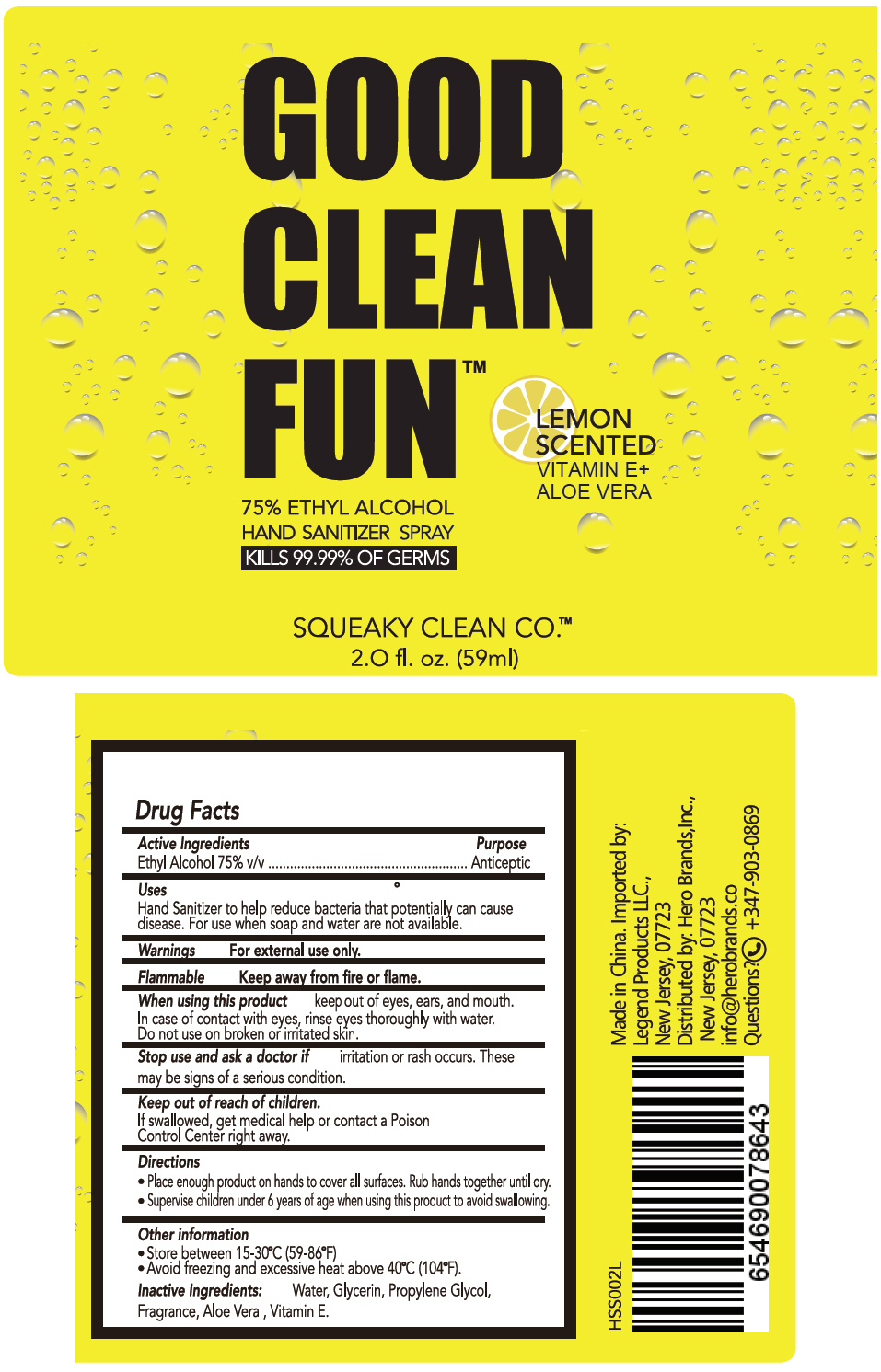 DRUG LABEL: Squeaky Clean Hand Sanitizer
NDC: 90114-101 | Form: LIQUID
Manufacturer: Hero Brands, Inc.
Category: otc | Type: HUMAN OTC DRUG LABEL
Date: 20200810

ACTIVE INGREDIENTS: Alcohol 75 mL/100 mL
INACTIVE INGREDIENTS: Water; Glycerin; Propylene Glycol; Aloe Vera Leaf; .ALPHA.-TOCOPHEROL

Squeaky Clean Hand Sanitizer

Drug Facts

Active Ingredients

Ethyl Alcohol 75% v/v

Purpose

Anticeptic

Uses

Hand Sanitizer to help reduce bacteria that potentially can cause disease. For use when soap and water are not available.

Warnings

For external use only.

Flammable

Keep away from fire or flame.

When using this product keep out of eyes, ears, and mouth. In case of contact with eyes, rinse eyes thoroughly with water. Do not use on broken or irritated skin.

Stop use and ask a doctor if irritation or rash occurs. These may be signs of a serious condition.

Keep out of reach of children.

If swallowed, get medical help or contact a Poison Control Center right away.

Directions

- Place enough product on hands to cover all surfaces. Rub hands together until dry.
- Supervise children under 6 years of age when using this product to avoid swallowing.

Other information

- Store between 15-30°C (59-86°F)
- Avoid freezing and excessive heat above 40°C (104°F).

Inactive Ingredients

Water, Glycerin, Propylene Glycol, Fragrance, Aloe Vera , Vitamin E.

Distributed by: Hero Brands,Inc.,
New Jersey, 07723

PRINCIPAL DISPLAY PANEL - 59 ml Bottle Label

GOOD
CLEAN
FUN™

LEMON
SCENTED
VITAMIN E+
ALOE VERA

75% ETHYL ALCOHOL
HAND SANITIZER SPRAY
KILLS 99.99% OF GERMS

SQUEAKY CLEAN CO.™

2.0 fl. oz. (59ml)